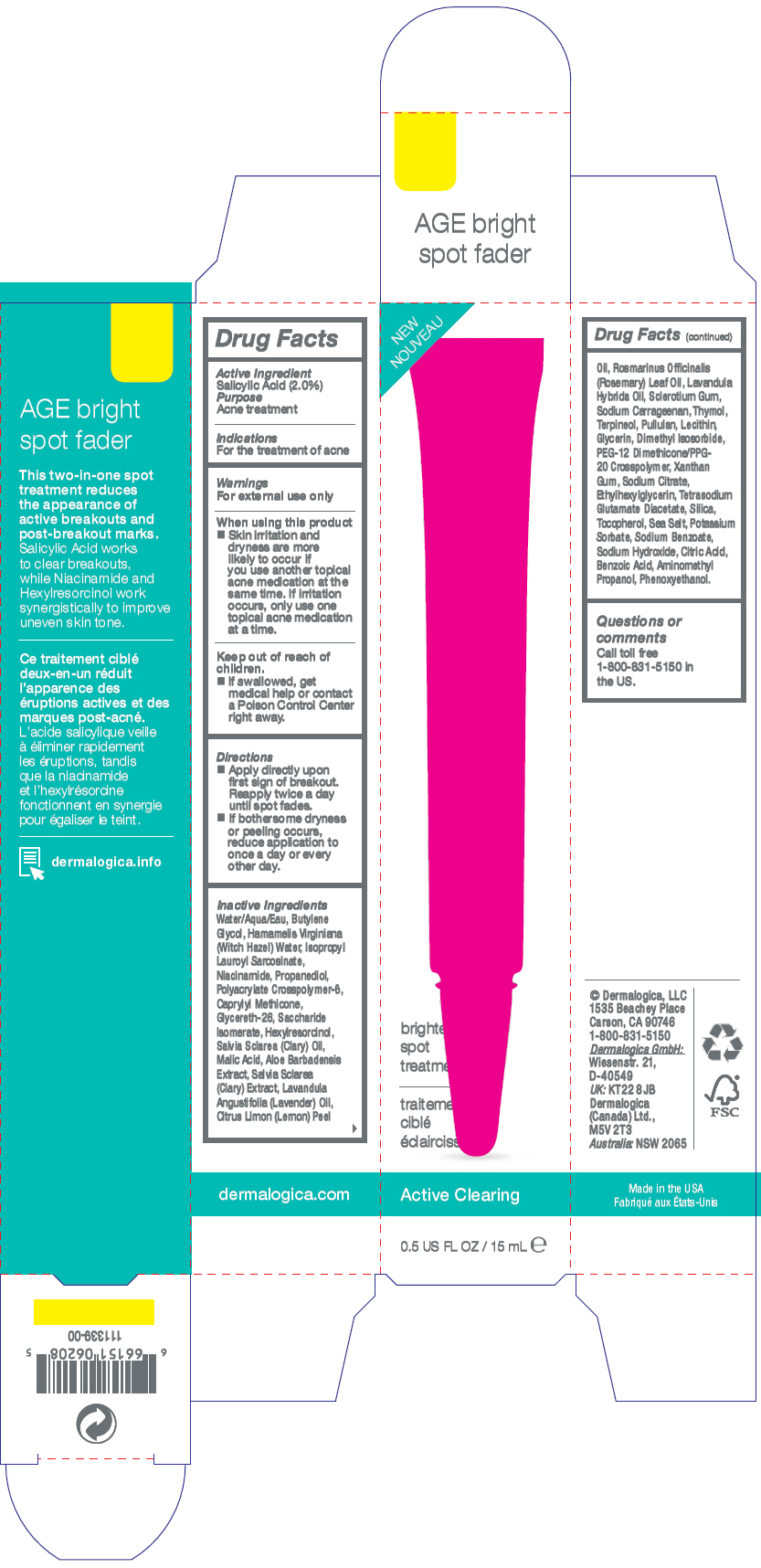 DRUG LABEL: AGE Bright Spot Fader
NDC: 68479-806 | Form: GEL
Manufacturer: Dermalogica, Inc
Category: otc | Type: HUMAN OTC DRUG LABEL
Date: 20190718

ACTIVE INGREDIENTS: Salicylic Acid 20 mg/1 mL
INACTIVE INGREDIENTS: Water; Butylene Glycol; HAMAMELIS VIRGINIANA TOP WATER; Isopropyl Lauroyl Sarcosinate; Niacinamide; Propanediol; AMMONIUM ACRYLOYLDIMETHYLTAURATE, DIMETHYLACRYLAMIDE, LAURYL METHACRYLATE AND LAURETH-4 METHACRYLATE COPOLYMER, TRIMETHYLOLPROPANE TRIACRYLATE CROSSLINKED (45000 MPA.S); CAPRYLYL TRISILOXANE; Glycereth-26; Saccharide Isomerate; Hexylresorcinol; CLARY SAGE OIL; Malic Acid; ALOE VERA LEAF; LAVENDER OIL; LEMON OIL; ROSEMARY OIL; LAVANDIN OIL; BETASIZOFIRAN; CARRAGEENAN SODIUM; Thymol; Terpineol; Pullulan; LECITHIN, SOYBEAN; Glycerin; Dimethyl Isosorbide; PEG-12 Dimethicone/PPG-20 Crosspolymer; Xanthan Gum; SODIUM CITRATE, UNSPECIFIED FORM; Ethylhexylglycerin; Tetrasodium Glutamate Diacetate; SILICON DIOXIDE; Tocopherol; Sea Salt; Potassium Sorbate; Sodium Benzoate; Sodium Hydroxide; CITRIC ACID MONOHYDRATE; Benzoic Acid; AMINOMETHYLPROPANOL; Phenoxyethanol

AGE Bright Spot Fader

Drug Facts

Active Ingredient

Salicylic Acid (2.0%)

Purpose

Acne treatment

Indications

For the treatment of acne

Warnings

For external use only

When using this product

- Skin irritation and dryness are more likely to occur if you use another topical acne medication at the same time. If irritation occurs, only use one topical acne medication at a time.

Keep out of reach of children.

- If swallowed, get medical help or contact a Poison Control Center right away.

Directions

- Apply directly upon first sign of breakout. Reapply twice a day until spot fades.
- If bothersome dryness or peeling occurs, reduce application to once a day or every other day.

Inactive Ingredients

Water/Aqua/Eau, Butylene Glycol, Hamamelis Virginiana (Witch Hazel) Water, Isopropyl Lauroyl Sarcosinate, Niacinamide, Propanediol, Polyacrylate Crosspolymer-6, Caprylyl Methicone, Glycereth-26, Saccharide Isomerate, Hexylresorcinol, Salvia Sclarea (Clary) Oil, Malic Acid, Aloe Barbadensis Extract, Salvia Sclarea (Clary) Extract, Lavandula Angustifolia (Lavender) Oil, Citrus Limon (Lemon) Peel Oil, Rosmarinus Officinalis (Rosemary) Leaf Oil, Lavandula Hybrida Oil, Sclerotium Gum, Sodium Carrageenan, Thymol, Terpineol, Pullulan, Lecithin, Glycerin, Dimethyl Isosorbide, PEG-12 Dimethicone/PPG-20 Crosspolymer, Xanthan Gum, Sodium Citrate, Ethylhexylglycerin, Tetrasodium Glutamate Diacetate, Silica, Tocopherol, Sea Salt, Potassium Sorbate, Sodium Benzoate, Sodium Hydroxide, Citric Acid, Benzoic Acid, Aminomethyl Propanol, Phenoxyethanol.

Questions or comments

Call toll free 1-800-831-5150 in the US.

PRINCIPAL DISPLAY PANEL - 15 mL Tube Carton

NEW

brightening
spot
treatment

Active Clearing

0.5 US FL OZ / 15 mL ℮